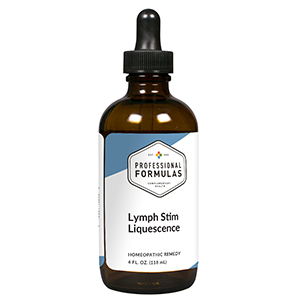 DRUG LABEL: Lymph Stim Liquescence
NDC: 63083-3016 | Form: LIQUID
Manufacturer: Professional Complementary Health Formulas
Category: homeopathic | Type: HUMAN OTC DRUG LABEL
Date: 20190815

ACTIVE INGREDIENTS: SCROPHULARIA NODOSA WHOLE 1 [hp_X]/118 mL; ECHINACEA ANGUSTIFOLIA WHOLE 2 [hp_X]/118 mL; ECHINACEA PURPUREA WHOLE 2 [hp_X]/118 mL; LEMON JUICE 3 [hp_X]/118 mL; SILICON DIOXIDE 3 [hp_X]/118 mL; PHYTOLACCA AMERICANA ROOT 4 [hp_X]/118 mL; THUJA OCCIDENTALIS LEAF 4 [hp_X]/118 mL; CAPSICUM 6 [hp_X]/118 mL; GOLDENSEAL 6 [hp_X]/118 mL; BOS TAURUS LYMPH VESSEL 6 [hp_X]/118 mL; SUS SCROFA MAMMARY GLAND 6 [hp_X]/118 mL; BOS TAURUS SPLEEN 6 [hp_X]/118 mL; HYSSOPUS OFFICINALIS WHOLE 6 [hp_X]/118 mL; ARSENIC TRIIODIDE 12 [hp_X]/118 mL; LACHESIS MUTA VENOM 12 [hp_X]/118 mL
INACTIVE INGREDIENTS: ALCOHOL; WATER

T16

ACTIVE INGREDIENTS

Scrophularia nodosa 1X
Echinacea angustifolia 2X
Echinacea purpurea 2X
Citrus limonum 3X
Silicea 3X, 6X, 12X
Phytolacca decandra 4X
Thuja occidentalis 4X
Capsicum annuum 6X
Hydrastis canadensis 6X
Lymph 6X
Mammary 6X
Spleen 6X
Thymus 6X
Arsenicum iodatum 12X
Lachesis mutus 12X

QUESTIONS

Professional Formulas

PO Box 2034 Lake Oswego, OR 97035

INDICATIONS

For the temporary relief of swelling of extremities, minor joint aches or discomfort, decreased flexibility, fatigue, or dry, itchy skin.*

PURPOSE

*Claims based on traditional homeopathic practice, not accepted medical evidence. Not FDA evaluated.

WARNINGS

Consult a doctor if condition worsens or if symptoms persist. Keep out of the reach of children. In case of overdose, get medical help or contact a poison control center right away. If pregnant or breastfeeding, ask a healthcare professional before use.

Keep out of the reach of children.

PREGNANCY OR BREAST FEEDING

If pregnant or breastfeeding, ask a healthcare professional before use.

DIRECTIONS

Place drops under tongue 30 minutes before/after meals. Adults and children 12 years and over: Take one full dropper up to 2 times per day. Consult a physician for use in children under 12 years of age.

OTHER INFORMATION

Tamper resistant. If seal is broken, do not use. After opening, close container tightly and store at room temperature away from heat.

INACTIVE INGREDIENTS

20% ethanol, purified water.

LABEL

Est 1985

Professional Formulas

Complementary Health

Lymph Stim Liquescence

Homeopathic Remedy

4 FL. OZ. (118 mL)